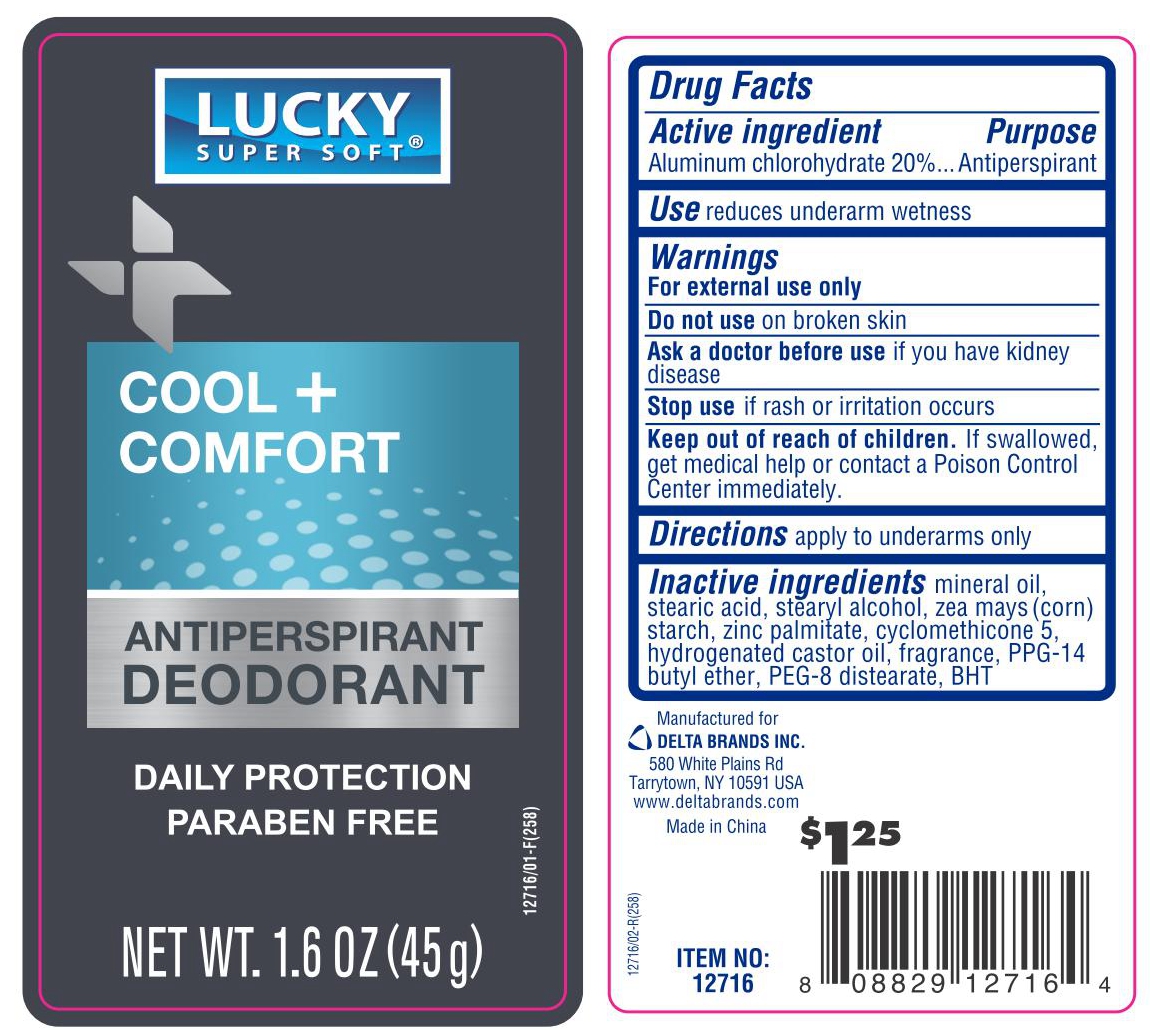 DRUG LABEL: LUCKY SUPER SOFT ANTIPERSPIRANT DEODORANT COOL COMFORT
NDC: 76176-019 | Form: STICK
Manufacturer: Ningbo Liyuan Daily Chemical Products Co., Ltd.
Category: otc | Type: HUMAN OTC DRUG LABEL
Date: 20240901

ACTIVE INGREDIENTS: ALUMINUM CHLOROHYDRATE 20 g/100 g
INACTIVE INGREDIENTS: STEARIC ACID; HYDROGENATED CASTOR OIL; STEARYL ALCOHOL; MINERAL OIL; CYCLOMETHICONE 5; PEG-8 DISTEARATE; BUTYLATED HYDROXYTOLUENE; ZINC PALMITATE; PPG-14 BUTYL ETHER

Active ingredient

Aluminum Chlorohydrate 20%

Purpose

Antiperspirant

Use

reduces underarm wetness

Warnings

For external use only

Do not use

on broken skin

Stop use

if rash or irritation occurs

Keep out of reach of children.

If swallowed, get medical help or contact a Poison Control Center immediately.

Directions

apply to underarms only

Inactive ingredients

mineral oil, stearic acid, stearyl alcohol, zea mays (corn) starch, zinc palmitate, cyclomethicone 5, hydrogenated castor oil, fragrance, PPG-14 butyl ether, PEG-8 distearate, BHT